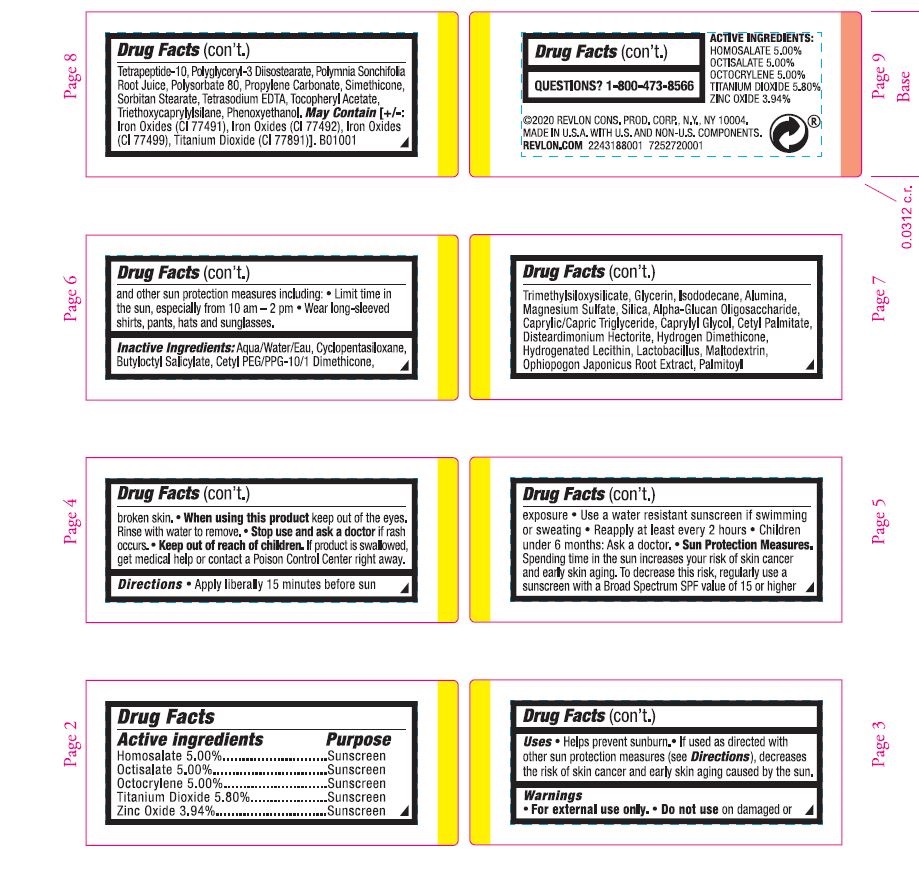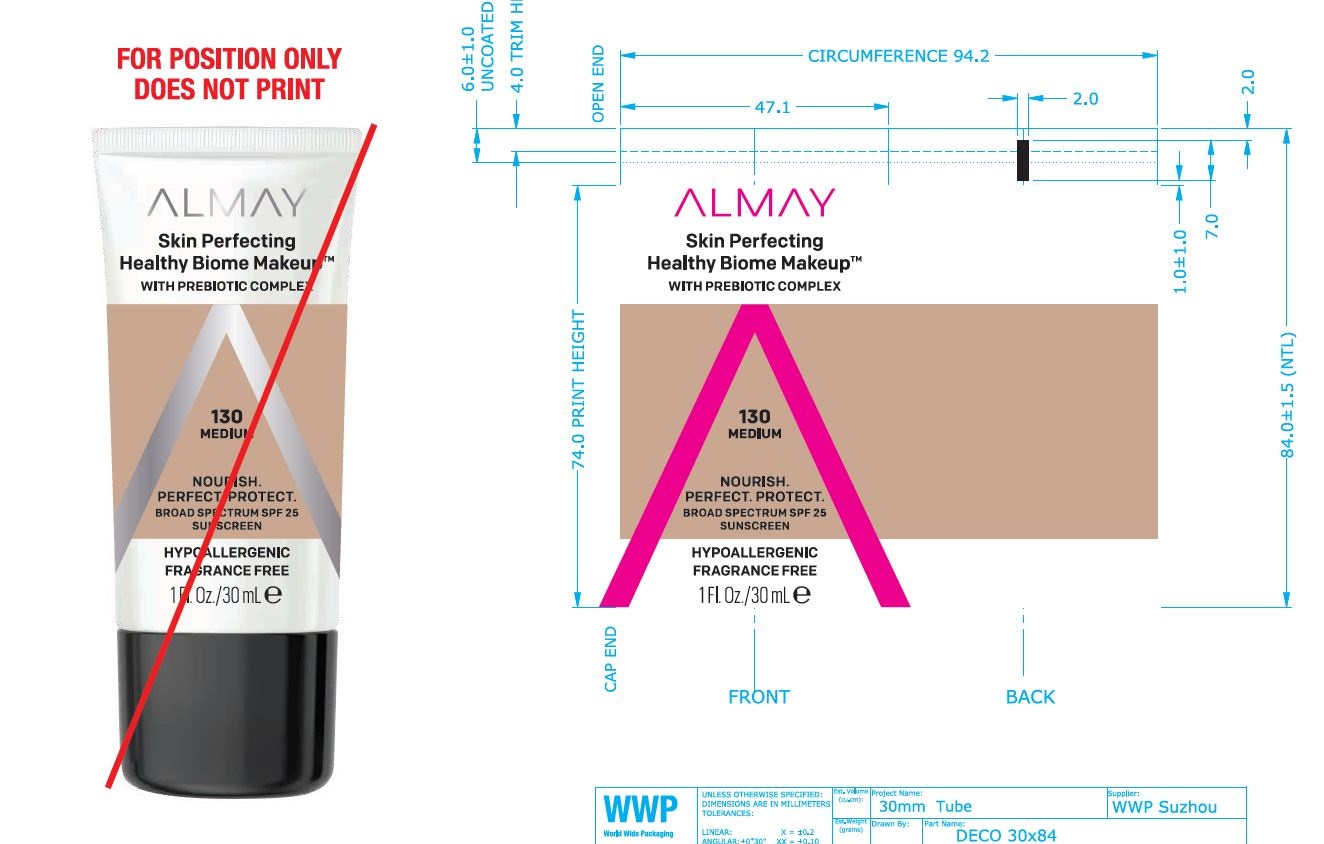 DRUG LABEL: Almay Healthy Biome Makeup
NDC: 0311-0739 | Form: EMULSION
Manufacturer: Almay
Category: otc | Type: HUMAN OTC DRUG LABEL
Date: 20241231

ACTIVE INGREDIENTS: HOMOSALATE 5 mg/1 mL; OCTISALATE 5 mg/1 mL; ZINC OXIDE 3.94 mg/1 mL; OCTOCRYLENE 5 mg/1 mL; TITANIUM DIOXIDE 5.8 mg/1 mL
INACTIVE INGREDIENTS: TRIMETHYLSILOXYSILICATE (M/Q 0.66); MAGNESIUM SULFATE ANHYDROUS; SILICON DIOXIDE; CETYL PALMITATE; DISTEARDIMONIUM HECTORITE; TRIETHOXYCAPRYLYLSILANE; PALMITOYL TETRAPEPTIDE-10; POLYSORBATE 80; .ALPHA.-TOCOPHEROL ACETATE, D-; PHENOXYETHANOL; .ALPHA.-GLUCAN OLIGOSACCHARIDE; DIMETHICONE; EDETATE SODIUM; DIMETHICONE CROSSPOLYMER (450000 MPA.S AT 12% IN CYCLOPENTASILOXANE); CETYL PEG/PPG-10/1 DIMETHICONE (HLB 2); HYDROGENATED SOYBEAN LECITHIN; CAPRYLYL GLYCOL; HYDROGEN DIMETHICONE (13 CST); MALTODEXTRIN; OPHIOPOGON JAPONICUS ROOT; WATER; GLYCERIN; BUTYLOCTYL SALICYLATE; ISODODECANE; ALUMINUM OXIDE; MEDIUM-CHAIN TRIGLYCERIDES; PROPYLENE CARBONATE; PEG-20 SORBITAN STEARATE; SMALLANTHUS SONCHIFOLIUS WHOLE; POLYGLYCERYL-3 DIISOSTEARATE

Almay Skin Perfacting Healthy Biome Makeup - MEDIUM

Active Ingredient Section

Homosalate 5.0%

Octisalate 5.0%

Octocrylene 5.0%

Titanium Dioxide 5.8%

Zinc Oxide 3.94%

Uses

Helps prevent sunburn. if used as directed with other sun protection measures descreases the risk of skin cancer and early skin aging caused by the sun.

Warnings

For external use only

Do not use on danaged skin or broken skin

Sun Protection Measures- Spending time in the sun increases your risk of skin cancer and early skin aging. To decrease this risk, regularly use a sunscreen with a Broad spectrum SPF value of 15 or higher and other sun protection measures including: limit time in the sun, especially from 10am- 2pm. Wear long-sleeved shrirts, pants, hats and sunglasses.

When using this product

Keep out of the eyes, Rinse with water to remove.

Stop use and ask a doctor if rash occurs.

Keep out of reach of children

If product is swalled get medical help or contact a Poison Control Center right away.

Directions

Apply liberally 15 minutes before sun exposure. Use water resistant sunscreen is swimming or sweating. Repply at least ever 2 hours. Children under 6 months; Ask a doctor.

INACTIVE INGREDIENT

Other Ingredients: Aqua/Water/Eau, Cyclopentasiloxane, Butyloctyl Salicylate, Cetyl PEG/PPG-10/1 Dimethicone, Trimethylsiloxysilicate, Glycerin, Isododecane, Alumina, Magnesium Sulfate, Silica, Alpha-Glucan Oligosaccharide, Caprylic/Capric Triglyceride, Caprylyl Glycol, Cetyl Palmitate, Disteardimonium Hectorite, Hydrogen Dimethicone, Hydrogenated Lecithin, Lactobacillus, Maltodextrin, Ophiopogon Japonicus Root Extract, Palmitoyl Tetrapeptide-10, Polyglyceryl-3 Diisostearate, Polymnia Sonchifolia Root Juice, Polysorbate 80, Propylene Carbonate, Simethicone, Sorbitan Stearate, Tetrasodium EDTA, Tocopheryl Acetate, Triethoxycaprylylsilane, Phenoxyethanol.

MAY CONTAIN/PEUT CONTENIR/PUEDE CONTENER (+/-):
[Iron Oxides (CI 77491),Iron Oxides (CI 77492),Iron Oxides (CI 77499),Titanium Dioxide (CI 77891).]

INDICATIONS AND USAGE

Helps prevent sunbunrs. If used as directed with other sun protection measures (See Directions), decreases the risk of skin cancer and early skin aging caused by the sun.